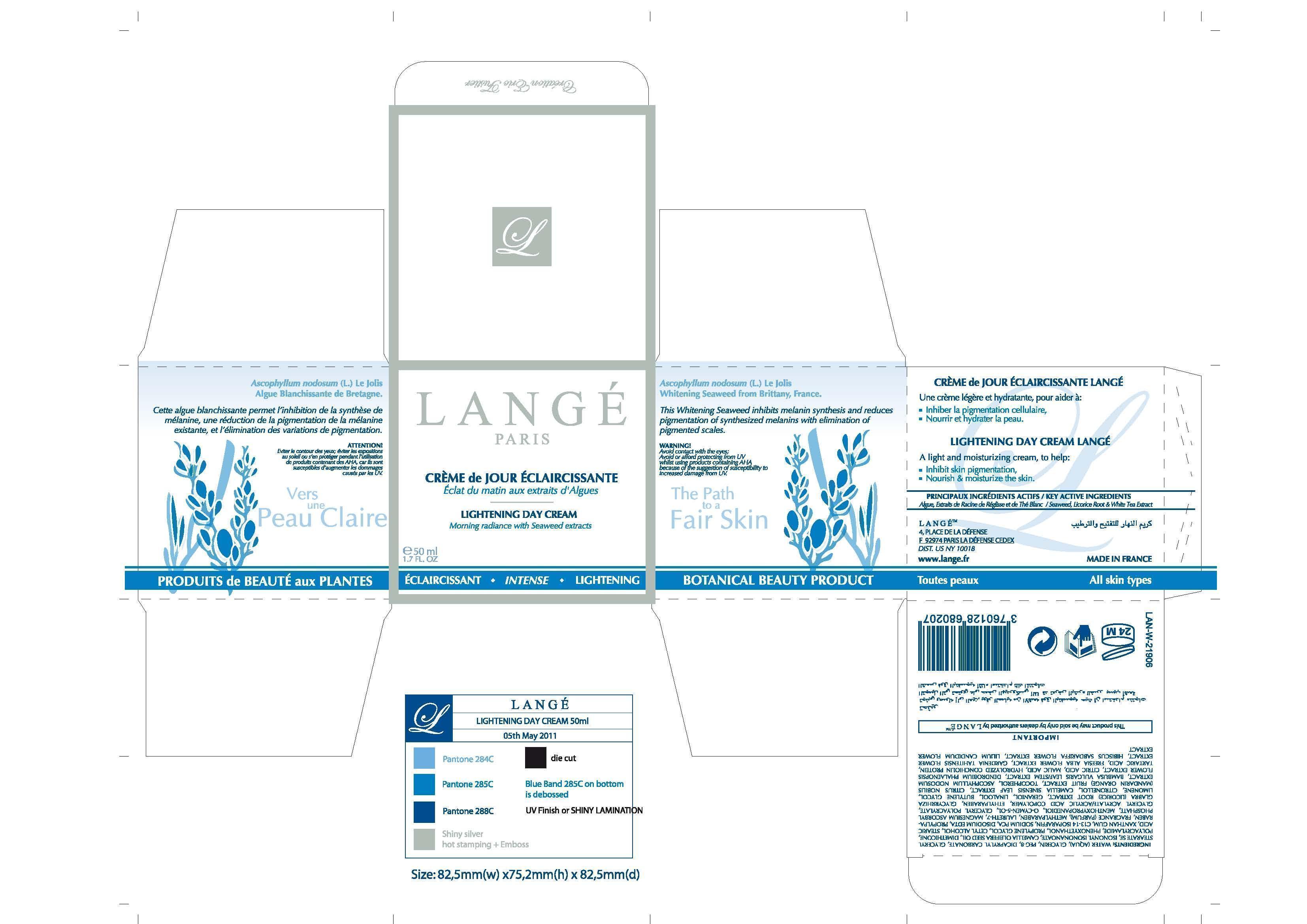 DRUG LABEL: Lightening Day Cream
NDC: 51830-019 | Form: CREAM
Manufacturer: LANGE SAS
Category: otc | Type: HUMAN OTC DRUG LABEL
Date: 20120718

ACTIVE INGREDIENTS: POLYETHYLENE GLYCOL 400 2.5 mg/50 mg
INACTIVE INGREDIENTS: DICAPRYLYL CARBONATE; WATER; GLYCERIN; POLYETHYLENE GLYCOL 400; GLYCERYL STEARATE SE; CAMELLIA KISSII SEED OIL; DIMETHICONE; PHENOXYETHANOL; PROPYLENE GLYCOL; CETYL ALCOHOL; STEARIC ACID; XANTHAN GUM; C13-14 ISOPARAFFIN; SODIUM PYRROLIDONE CARBOXYLATE; EDETATE DISODIUM; PROPYLPARABEN; METHYLPARABEN; LAURETH-7; 3-((L-MENTHYL)OXY)PROPANE-1,2-DIOL; O-CYMEN-5-OL; ETHYLPARABEN; GLYCYRRHIZA GLABRA; BUTYLENE GLYCOL; POLYACRYLAMIDE (10000 MW); GLYCERIN; ACRYLIC ACID; MAGNESIUM ASCORBYL PHOSPHATE; ISONONYL ISONONANOATE

KEY ACTIVE INGREDIENTS
Seaweed, Licorice Root and White Tea Extract

PURPOSE

This Whitening Seaweed inhibits melanin synthesis and reduces pigmentation of synthesized melanins with elimination of pigmented scales.

Keep out of reach of children.

INDICATIONS AND USAGE

LIGHTENING DAY CREAM LANGE
A light and moisturizing cream, to help:
Inhibit skin pigmentation,
Nourish and moisturize the skin.

WARNING!
Avoid contact with the eyes;
Avoid or afford protecting from UV
whilst using products containing AHA
because of the suggestion of susceptibility to
increased damage from UV.

DOSAGE AND ADMINISTRATION

50 mL
1.7 FL. OZ

INACTIVE INGREDIENT

WATER (AQUA)
GLYCERIN
PEG-8
DICAPRYLYL CARBONATE
GLYCERYL STEARATE SE
ISONONYL ISONONANOATE
CAMELLIA KISSI SEED OIL
DIMETHICONE
POLYACRYLAMIDE
PHENOXYETHANOL
PROPYLENE GLYCOL
CETYL ALCOHOL
STEARIC ACID
XANTHAN GUM
C13-14 ISOPARAFFIN
SODIUM PCA
DISODIUM EDTA
PROPYLPARABEN
METHYLPARABEN
LAURETH-7
MAGNESIUM ASCORBYL PHOSPHATE
MENTHOXYPROPANEDIOL
o-CYMEN-5-OL
GLYCERYL POLYACRYLATE
GLYCERYL ACRYLATE/ACRYLIC ACID COPOLYMER
ETHYLPARABEN
GLYCYRRHIZA GLABRA (LICORICE) ROOT EXTRACT
BUTYLENE GLYCOL

PACKAGE LABEL

LANGE
PARIS
LIGHTENING DAY CREAM
Morning radiance with Seaweed extracts
50 ml
1.7 FL. OZ